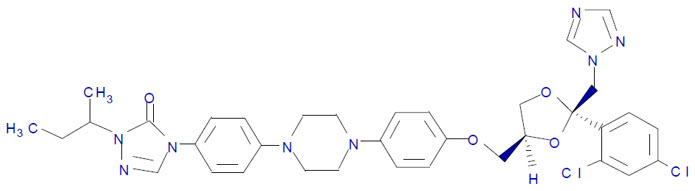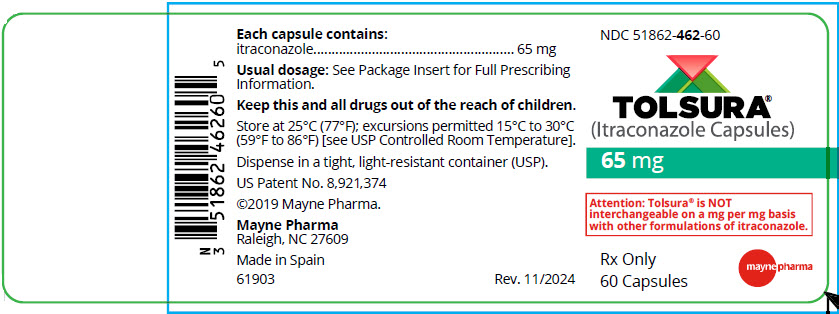 DRUG LABEL: Tolsura
NDC: 51862-462 | Form: CAPSULE, GELATIN COATED
Manufacturer: Mayne Pharma Commercial LLC
Category: prescription | Type: HUMAN PRESCRIPTION DRUG LABEL
Date: 20250423

ACTIVE INGREDIENTS: ITRACONAZOLE 65 mg/1 1
INACTIVE INGREDIENTS: HYPROMELLOSE PHTHALATE (24% PHTHALATE, 55 CST); SODIUM STARCH GLYCOLATE TYPE A POTATO; SILICON DIOXIDE; MAGNESIUM STEARATE; METHYLENE CHLORIDE; FD&C BLUE NO. 1; TITANIUM DIOXIDE; GELATIN, UNSPECIFIED

HIGHLIGHTS OF PRESCRIBING INFORMATION

These highlights do not include all the information needed to use TOLSURA® safely and effectively. See full prescribing information for TOLSURA®.
TOLSURA® (itraconazole capsules), for oral use
Initial U.S. Approval: 1992

WARNING: CONGESTIVE HEART FAILURE and DRUG INTERACTIONS

See full prescribing information for complete boxed warning.

- Congestive Heart Failure
  TOLSURA can cause or exacerbate congestive heart failure (CHF). When itraconazole was administered intravenously to healthy human volunteers and dogs, negative inotropic effects were seen. If signs or symptoms of congestive heart failure occur or worsen during administration of TOLSURA, reassess the benefit-risk of continuing treatment. (5.1, 6).
- Drug Interactions
  - Co-administration of certain drugs that are metabolized by human CYP3A4 enzymes are contraindicated with TOLSURA because plasma concentrations of such drugs are increased. (4.1, 5.5, 7.1)
  - Co-administration with colchicine, fesoterodine and solifenacin is contraindicated in subjects with varying degrees of renal or hepatic impairment. (4.1, 7.1)
  - Co-administration with eliglustat is contraindicated in poor or intermediate metabolizers of CYP2D6 and in subjects taking strong or moderate CYP2D6 inhibitors. (4.1, 7.1)
  - Increased plasma concentrations of some of these drugs can lead to QT prolongation and ventricular tachyarrhythmias including occurrences of torsades de pointes, a potentially fatal arrhythmia. (4.1, 5.5, 7.1)

RECENT MAJOR CHANGES

Warnings and Precautions, Pseudoaldosteronism (5.4) | 10/2024

1 INDICATIONS AND USAGE

TOLSURA is an azole antifungal indicated for the treatment of the following fungal infections in immunocompromised and non-immunocompromised adult patients (1):

- Blastomycosis, pulmonary and extrapulmonary
- Histoplasmosis, including chronic cavitary pulmonary disease and disseminated, non-meningeal histoplasmosis, and
- Aspergillosis, pulmonary and extrapulmonary, in patients who are intolerant of or who are refractory to amphotericin B therapy.

Limitations of Use:

TOLSURA is not indicated for the treatment of onychomycosis (1)

TOLSURA is NOT interchangeable or substitutable with other itraconazole products (1)

2 DOSAGE AND ADMINISTRATION

- Blastomycosis and Histoplasmosis - 130 mg to 260 mg daily (2)
- Aspergillosis - 130 mg to 260 mg daily (2)
- See full prescribing information for additional dosing for life-threatening situations. (2)
- TOLSURA must be administered with food. (2)
- Swallow whole. Do not chew crush or break. (2)

3 DOSAGE FORMS AND STRENGTHS

Capsules: 65 mg (3)

4 CONTRAINDICATIONS

- Co-administration with certain drugs that either affect metabolism of itraconazole or whose metabolism is affected by itraconazole. (4.1)
- Hypersensitivity to itraconazole (4.2)

5 WARNINGS AND PRECAUTIONS

- Hepatotoxicity: Serious hepatotoxicity, including liver failure and death were reported with the use of itraconazole. Discontinue treatment if signs of liver dysfunction occur (5.2)
- Cardiac Dysrhythmias: Life-threatening cardiac dysrhythmias and/or sudden death have occurred in patients using certain drugs that are metabolized by human CYP450 enzymes concomitantly with oral itraconazole and/or other CYP3A4 inhibitors. (4, 5.3, 5.5)
- Pseudoaldosteronism: Manifested by the onset or worsening of hypertension, and abnormal laboratory findings. Monitor blood pressure and potassium levels and manage as necessary (5.4).
- Peripheral Neuropathy: This has been reported in patients on long-term therapy with itraconazole. Monitor and promptly evaluate neurologic symptoms. (5.6)
- Hearing Loss: Reversible or permanent has been reported in patients. Discontinue treatment if hearing loss occurs (5.7)

6 ADVERSE REACTIONS

Most common adverse reactions (incidence ≥ 1%) are nausea, rash, vomiting, edema, headache, diarrhea, fatigue, fever, pruritus, hypertension, abnormal hepatic function, abdominal pain, dizziness, hypokalemia, anorexia, malaise, decreased libido, somnolence, albuminuria, impotence (6.1)

To report SUSPECTED ADVERSE REACTIONS, contact Mayne Pharma at 1-844-825-8500 or FDA at 1-800-FDA-1088 or www.fda.gov/medwatch.

7 DRUG INTERACTIONS

Itraconazole is mainly metabolized through CYP3A4. Other drugs that either share this metabolic pathway or modify CYP3A4 activity may influence the pharmacokinetics of itraconazole. (4, 5, 7.1, 7.2)

FULL PRESCRIBING INFORMATION

WARNING: CONGESTIVE HEART FAILURE and DRUG INTERACTIONS

- Congestive Heart Failure
  TOLSURA can cause or exacerbate congestive heart failure (CHF). When itraconazole was administered intravenously to healthy human volunteers and dogs, negative inotropic effects were seen. If signs or symptoms of congestive heart failure occur or worsen during administration of TOLSURA, reassess the benefit and risk of continuing treatment [see Warnings and Precautions (5.1) and Adverse Reactions (6.1)].

- Drug Interactions
  - Co-administration of certain drugs that are metabolized by human CYP3A4 enzymes are contraindicated with TOLSURA because plasma concentrations of such drugs are increased, which may also increase or prolong both the pharmacologic effects and/or adverse reactions to these drugs [see Contraindications (4.1) and Drug Interactions (7.1)]
  - Co-administration with colchicine, fesoterodine and solifenacin is contraindicated in subjects with varying degrees of renal or hepatic impairment, and
  - Co-administration with eliglustat is contraindicated in subjects that are poor or intermediate metabolizers of CYP2D6 and in subjects taking strong or moderate CYP2D6 inhibitors.
  - Increased plasma concentrations of some of these drugs caused by co-administration with TOLSURA can lead to QT prolongation and/or ventricular tachyarrhythmias, including occurrences of torsades de pointes, a potentially fatal arrhythmia [see Contraindications (4.1), Warnings and Precautions (5.5) and Drug Interactions (7.1)].

1 INDICATIONS AND USAGE

TOLSURA is indicated for the treatment of the following fungal infections in immunocompromised and non-immunocompromised adult patients:

- Blastomycosis, pulmonary and extrapulmonary
- Histoplasmosis, including chronic cavitary pulmonary disease and disseminated, non-meningeal histoplasmosis, and
- Aspergillosis, pulmonary and extrapulmonary, in patients who are intolerant of or who are refractory to amphotericin B therapy.

Specimens for fungal cultures and other relevant laboratory studies (wet mount, histopathology, serology) should be obtained before therapy to isolate and identify causative organisms. Therapy may be instituted before the results of the cultures and other laboratory studies are known; however, once these results become available, anti-fungal therapy should be adjusted accordingly

Limitations of Use:

TOLSURA is not indicated for the treatment of onychomycosis.

TOLSURA is NOT interchangeable or substitutable with other itraconazole products due to the differences in the dosing between TOLSURA and other itraconazole products. Therefore, follow the specific dosage recommendations for TOLSURA [see Dosage and Administration (2)].

2 DOSAGE AND ADMINISTRATION

TOLSURA must be administered with food.

TOLSURA capsules must be swallowed whole. Do not chew, crush or break TOLSURA capsules.

Table 1 below describes the recommended dosage for TOLSURA.

Table 1: Dosage and Administration of TOLSURA
Indications | Daily Dosing
Treatment of Blastomycosis and Histoplasmosis
Recommended dose | 130 mg (2 × 65 mg capsules) once daily If no obvious improvement, or there is evidence of progressive fungal disease, the dose should be increased in 65 mg increments to a maximum of 260 mg/day (130 mg (2 × 65 mg capsules) twice daily). Doses above 130 mg/day should be given in two divided doses.
Treatment of Aspergillosis
Recommended dose | 130 mg (2 × 65 mg capsules) once daily
Recommended dose | 260 mg/day (130 mg (2 × 65 mg capsules) twice daily)
Treatment in Life-Threatening Situations
Although clinical studies did not provide for a loading dose, it is recommended, based on pharmacokinetic data, that a loading dose should be used. | A loading dose of 130 mg (2 × 65 mg capsules) three times daily (390 mg/day) is recommended to be given for the first 3 days, followed by the appropriate recommended dosing based on indication. Treatment should be continued for a minimum of three months and until clinical parameters and laboratory tests indicate that the active fungal infection has subsided. An inadequate period of treatment may lead to recurrence of active infection.

3 DOSAGE FORMS AND STRENGTHS

TOLSURA (itraconazole capsules) is available in a size 1, hard gelatin capsules with light blue cap and white body, imprinted with "i-65" in black on the cap and containing 65 mg of itraconazole.

4 CONTRAINDICATIONS

4.1 Drug Interactions

- Co-administration of certain drugs that are metabolized by human CYP3A4 substrates are contraindicated with TOLSURA because plasma concentrations of such drugs are increased, which may also increase or prolong both the pharmacologic effects and/or adverse reactions to these drugs [see Warnings and Precaution (5.5) and Drug Interactions (7.1)].
- Co-administration with colchicine, fesoterodine and solifenacin is contraindicated in subjects with varying degrees of renal or hepatic impairment.
- Co-administration with eliglustat is contraindicated in subjects that are poor or intermediate metabolizers of CYP2D6 and in subjects taking strong or moderate CYP2D6 inhibitors [see Drug Interactions (7.1)].
- Increased plasma concentrations of some of these drugs due to co-administration of TOLSURA can lead to QT prolongation and ventricular tachyarrhythmias including occurrences of torsade de pointes, a potentially fatal arrhythmia [see Drug Interactions (7.1)].

4.2 Hypersensitivity

TOLSURA is contraindicated in patients with known hypersensitivity to itraconazole. There is limited information regarding cross-hypersensitivity between itraconazole and other azole antifungal agents [see Warnings and Precautions (5.8)].

5 WARNINGS AND PRECAUTIONS

5.1 Congestive Heart Failure

TOLSURA can cause or exacerbate congestive heart failure (CHF) [see Boxed Warning and Adverse Reactions (6.1)]. For patients with evidence of ventricular dysfunction such as CHF, history or risk factors for CHF, physicians should carefully review the risks and benefits of TOLSURA therapy. These risk factors include cardiac disease such as ischemic and valvular disease; significant pulmonary disease such as chronic obstructive pulmonary disease; and renal failure and other edematous disorders. Inform such patients of the signs and symptoms of CHF and monitor carefully for signs and symptoms of CHF during treatment. If signs or symptoms of CHF appear or worsen during administration of TOLSURA, reassess the benefit-risk of continuing treatment.

When itraconazole was administered intravenously to anesthetized dogs, a dose-related negative inotropic effect was demonstrated. In a healthy volunteer study of itraconazole intravenous infusion, transient, asymptomatic decreases in left ventricular ejection fraction were observed using gated SPECT imaging; these resolved before the next infusion, 12 hours later.

Itraconazole has been associated with reports of CHF, peripheral edema, and pulmonary edema. In post-marketing experience, heart failure was more frequently reported in patients receiving higher total daily doses of itraconazole of 400 mg although there were also cases reported among those receiving lower total daily doses [see Adverse Reactions (6.2)].

Calcium channel blockers can have negative inotropic effects which may be additive to those of itraconazole. In addition, itraconazole can inhibit the metabolism of calcium channel blockers. Therefore, when co-administering itraconazole and calcium channel blockers, monitor carefully for signs and symptoms of CHF during treatment due to an increased risk of CHF. Concomitant administration of TOLSURA and felodipine or nisoldipine is contraindicated [see Contraindications (4.1), Drug Interactions (7.1) and Adverse Reactions (6.2)]

5.2 Hepatotoxicity

Itraconazole has been associated with cases of serious hepatotoxicity, including liver failure and death. Some of these cases had neither pre-existing liver disease nor a serious underlying medical condition, and some of these cases developed within the first week of treatment. If clinical signs or symptoms develop that are consistent with liver disease, discontinue treatment and perform testing for liver disease. Continued TOLSURA use or reinstitution of treatment with TOLSURA is strongly discouraged unless there is a serious or life-threatening situation where the expected benefit exceeds the risk [see Adverse Reactions (6.1)].

5.3 Cardiac Dysrhythmias

Life-threatening cardiac dysrhythmias and/or sudden death have occurred in patients using drugs such as, pimozide, methadone, or quinidine concomitantly with oral itraconazole and/or other CYP3A4 inhibitors. Concomitant administration of these drugs with TOLSURA is contraindicated [see Boxed Warning, Contraindications (4) and Drug Interactions (7)].

5.4 Pseudoaldosteronism

Pseudoaldosteronism, manifested by the onset of hypertension or worsening of hypertension, and abnormal laboratory findings (hypokalemia, low serum renin and aldosterone, and elevate 11-deoxycortisol), has been reported with itraconazole use in the postmarketing setting. Monitor blood pressure and potassium levels and manage as necessary. Management of pseudoaldosteronism may include discontinuation of TOLSURA, substitution with an appropriate antifungal drug that is not associated with pseudoaldosteronism, or use of aldosterone receptor antagonists.

5.5 Drug Interaction Potential

Itraconazole has a potential for clinically important drug interactions [see Drug Interactions (7.1, 7.2)]. Co-administration of specific drugs with TOLSURA may result in changes in the efficacy of itraconazole and/or the co-administered drug, life-threatening effects and/or sudden death. [see Boxed Warning, Contraindications (4.1) and Drug Interactions (7.1, 7.2)].

5.6 Peripheral Neuropathy

Cases of peripheral neuropathy have been reported in patients on long-term therapy with itraconazole. Monitor for and promptly evaluate neurologic symptoms. If neuropathy attributable to TOLSURA occurs, discontinue treatment.

5.7 Hearing Loss

Reversible or permanent hearing loss has been reported in patients receiving treatment with itraconazole. Several of these reports included concurrent administration of quinidine which is contraindicated [see Boxed Warning, Contraindications (4.2) and Drug Interactions (7)]. The hearing loss usually resolves when treatment is stopped but can persist in some patients.

5.8 Hypersensitivity Reactions

TOLSURA is contraindicated in patients with a known hypersensitivity to itraconazole [see Contraindications (4.2)]. Hypersensitivity reactions have been reported with the use of itraconazole [see Adverse Reactions (6.2)]. Due to the limited information regarding cross-hypersensitivity between itraconazole and other azole antifungal drugs, careful enquiry about previous hypersensitivity to other azole antifungal drugs should be made when prescribing TOLSURA. If hypersensitivity reactions to TOLSURA occurs, discontinue the drug and institute appropriate therapy.

6 ADVERSE REACTIONS

The following clinically significant adverse reactions are described elsewhere in the labeling:

- Congestive Heart Failure [see Warnings and Precautions (5.1)]
- Hepatotoxicity [see Warnings and Precautions (5.2)]
- Cardiac Dysrhythmias [see Warnings and Precautions (5.3)]
- Pseudoaldosteronism [see Warnings and Precautions (5.4)]
- Peripheral Neuropathy [see Warnings and Precautions (5.6)]
- Hearing Loss [see Warnings and Precautions (5.7)]
- Hypersensitivity Reactions [see Warnings and Precautions (5.8)]

6.1 Clinical Trials Experience

Because clinical trials are conducted under widely varying conditions, adverse reaction rates observed in the clinical trials of a drug cannot be directly compared to rates in the clinical trials of another drug and may not reflect the rates observed in clinical practice.

Adverse Reactions in the Treatment of Systemic Fungal Infections

Safety data with itraconazole capsules were derived from 602 patients treated for systemic fungal disease in U.S. clinical trials who were immunocompromised or receiving multiple concomitant medications. Treatment was discontinued in 10.5% of patients due to adverse events. The median duration before discontinuation of therapy was 81 days (range: 2 to 776 days). Table 2 lists adverse reactions reported by at least 1% of patients.

Table 2: Clinical Trials of Systemic Fungal Infections: Adverse Reactions Occurring with an Incidence of ≥1%
Body System/Adverse Reaction | Incidence (%) (N=602)
Gastrointestinal
Nausea | 11
Vomiting | 5
Diarrhea | 3
Abdominal Pain | 2
Anorexia | 1
Body as a Whole
Edema | 4
Fatigue | 3
Fever | 3
Malaise | 1
Skin and Appendages
Rash [Rash tends to occur more frequently in immunocompromised patients receiving immunosuppressive medications.] | 9
Pruritus | 3
Central/Peripheral Nervous System
Headache | 4
Dizziness | 2
Psychiatric
Libido Decreased | 1
Somnolence | 1
Cardiovascular
Hypertension | 3
Metabolic/Nutritional
Hypokalemia | 2
Urinary System
Albuminuria | 1
Liver and Biliary System
Hepatic Function Abnormal | 3
Reproductive System, Male
Impotence | 1

Adverse reactions reported at a rate of <1% included: constipation, gastritis, depression, insomnia, tinnitus, menstrual disorder, adrenal insufficiency, gynecomastia, and male breast pain.

Adverse Reactions Reported from Other Clinical Trials

In addition, the following adverse reactions were reported in itraconazole-treated patients who participated in clinical trials:

Hepatobiliary Disorders: hyperbilirubinemia;

Cardiac Disorders: cardiac failure, left ventricular failure, tachycardia;

General Disorders and Administration Site Conditions: face edema, chest pain, chills;

Hepatobiliary Disorders: hepatic failure, jaundice;

Investigations: alanine aminotransferase increased, aspartate aminotransferase increased, blood alkaline phosphatase increased, blood lactate dehydrogenase increased, blood urea increased, gammaglutamyltransferase increased, urine analysis abnormal;

Metabolism and Nutrition Disorders: hyperglycemia, hyperkalemia, hypomagnesemia;

Psychiatric Disorders: confusional state;

Renal and Urinary Disorders: renal impairment;

Respiratory, Thoracic and Mediastinal Disorders: dysphonia, cough;

Skin and Subcutaneous Tissue Disorders: hyperhidrosis;

Vascular Disorders: hypotension

6.2 Postmarketing Experience

Adverse reactions that have been identified during post-marketing experience with itraconazole are listed in Table 3. Because these reactions are reported voluntarily from a population of uncertain size, reliably estimating their frequency or establishing a causal relationship to drug exposure is not always possible.

Table 3: Postmarketing Reports of Adverse Drug Reactions
Blood and Lymphatic System Disorders: | Leukopenia, neutropenia, thrombocytopenia
Immune System Disorders: | Anaphylaxis; anaphylactic, anaphylactoid and allergic reactions; serum sickness; angioneurotic edema
Endocrine Disorders: | Pseudoaldosteronism
Nervous System Disorders: | Peripheral neuropathy, paresthesia, hypoesthesia, tremor
Eye Disorders: | Visual disturbances, including blurred vision and diplopia
Ear and Labyrinth Disorders: | Transientor permanent hearing loss
Respiratory, Thoracic and Mediastinal Disorders: | Pulmonary edema, dyspnea
Gastrointestinal Disorders: | Pancreatitis, dysgeusia
Hepatobiliary Disorders: | Serious hepatotoxicity (including some cases of fatal acute liver failure), hepatitis
Skin and Subcutaneous Tissue Disorders: | Toxic epidermal necrolysis, Stevens-Johnson syndrome, acute generalized exanthematous pustulosis, erythema multiforme, exfoliative dermatitis, leukocytoclastic vasculitis, alopecia, photosensitivity, urticaria
Musculoskeletal and Connective Tissue Disorders: | Arthralgia
Renal and Urinary Disorders: | Urinary incontinence, pollakiuria
Reproductive System and Breast Disorders: | Erectile dysfunction
General Disorders and Administration Site Conditions: | Peripheral edema
Investigations: | Blood creatine phosphokinase increased

7 DRUG INTERACTIONS

7.1 Effect of TOLSURA on Other Drugs

Itraconazole and its major metabolite, hydroxy-itraconazole, are potent CYP3A4 inhibitors. Itraconazole is an inhibitor of the drug transporters P-glycoprotein and breast cancer resistance protein (BCRP). Consequently, itraconazole has the potential to interact with many concomitant drugs resulting in either increased or sometimes decreased concentrations of the concomitant drugs. Increased concentrations may increase the risk of adverse reactions associated with the concomitant drug which can be severe or life-threatening in some cases (e.g., QT prolongation, Torsade de Pointes, respiratory depression, hepatic adverse reactions, hypersensitivity reactions, myelosuppression, hypotension, seizures, angioedema, atrial fibrillation, bradycardia, priapism). Reduced concentrations of concomitant drugs may reduce their efficacy. Table 4 lists examples of drugs that may have their concentrations affected by itraconazole, but is not a comprehensive list. Refer to the approved product labeling to become familiar with the interaction pathways, risk potential, and specific actions to be taken with regards to each concomitant drug prior to initiating therapy with itraconazole.

Although many of the clinical drug interactions in Table 4 are based on information with a similar azole antifungal, ketoconazole, these interactions are expected to occur with itraconazole.

Table 4: Drug Interactions with TOLSURA that Affect Concomitant Drug Concentrations
Concomitant Drug Within Class |  | Prevention or Management
Drug Interactions with TOLSURA that Increase Concomitant Drug Concentrations and May Increase Risk of Adverse Reactions Associated with the Concomitant Drug
Alpha Blockers
Alfuzosin Silodosin Tamsulosin |  | Not recommended during and 2 weeks after TOLSURA treatment.
Analgesics
Methadone |  | Contraindicated during and 2 weeks after TOLSURA treatment.
Fentanyl |  | Not recommended during and 2 weeks after TOLSURA treatment.
Alfentanil Buprenorphine (IV and sublingual) Oxycodone [Based on clinical drug interaction information with itraconazole.] Sufentanil |  | Monitor for adverse reactions. Concomitant drug dose reduction may be necessary.
Antiarrhythmics
Disopyramide Dofetilide Dronedarone Quinidine |  | Contraindicated during and 2 weeks after TOLSURA treatment.
Digoxin |  | Monitor for adverse reactions. Concomitant drug dose reduction may be necessary.
Antibacterials
Bedaquiline [Based on 400 mg Bedaquiline once daily for 2 weeks.] |  | Concomitant TOLSURA not recommended for more than 2 weeks at any time during bedaquiline treatment.
Rifabutin |  | Not recommended 2 weeks before, during, and 2 weeks after TOLSURA treatment. See also Table 5.
Clarithromycin |  | Monitor for adverse reactions. Concomitant drug dose reduction may be necessary. See also Table 5.
Trimetrexate |  | Monitor for adverse reactions. Concomitant drug dose reduction may be necessary.
Anticoagulants and Antiplatelets
Ticagrelor |  | Contraindicated during and 2 weeks after TOLSURA treatment.
Apixaban Rivaroxaban Vorapaxar |  | Not recommended during and 2 weeks after TOLSURA treatment.
Cilostazol Dabigatran Warfarin |  | Monitor for adverse reactions. Concomitant drug dose reduction may be necessary.
Anticonvulsants
Carbamazepine |  | Not recommended 2 weeks before, during, and 2 weeks after TOLSURA treatment. See also Table 5.
Antidiabetic Drugs
Repaglinide Saxagliptin |  | Monitor for adverse reactions. Concomitant drug dose reduction may be necessary.
Antihelminthics, Antifungals and Antiprotozoals
Isavuconazonium |  | Contraindicated during and 2 weeks after TOLSURA treatment.
Praziquantel |  | Monitor for adverse reactions. Concomitant drug dose reduction may be necessary.
Artemether-lumefantrine Quinine |  | Monitor for adverse reactions.
Antimigraine Drugs
Ergot alkaloids (e.g., dihydroergotamine, ergotamine) |  | Contraindicated during and 2 weeks after TOLSURA treatment.
Eletriptan |  | Monitor for adverse reactions. Concomitant drug dose reduction may be necessary
Antineoplastics
Irinotecan |  | Contraindicated during and 2 weeks after TOLSURA treatment.
Axitinib Bosutinib Cabazitaxel Cabozantinib Ceritinib Cobimetinib Crizotinib Dabrafenib Dasatinib | Docetaxel Ibrutinib Lapatinib Nilotinib Olaparib Pazopanib Sunitinib Trabectedin Trastuzumab-emtansine Vinca alkaloids | Not recommended during and 2 weeks after TOLSURA treatment.
Bortezomib Brentuximab-vedotin Busulfan Erlotinib Gefitinib Idelalisib Imatinib Ixabepilone | Nintedanib Panobinostat Ponatinib Ruxolitinib Sonidegib Vandetanib | Monitor for adverse reactions. Concomitant drug dose reduction may be necessary. For Idelalisib, see also Table 5.
Antipsychotics, Anxiolytics and Hypnotics
Alprazolam Aripiprazole Buspirone Diazepam Haloperidol | Midazolam (IV) Quetiapine Ramelteon Risperidone Suvorexant | Monitor for adverse reactions. Concomitant drug dose reduction may be necessary.
Zopiclone |  | Monitor for adverse reactions. Concomitant drug dose reduction may be necessary.
Lurasidone Midazolam (oral) Pimozide Triazolam |  | Contraindicated during and 2 weeks after TOLSURA treatment.
Antivirals
Simeprevir |  | Not recommended during and 2 weeks after TOLSURA treatment.
Daclatasvir Indinavir Maraviroc |  | Monitor for adverse reactions. Concomitant drug dose reduction may be necessary. For indinavir, see also Table 5.
Cobicistat Elvitegravir (ritonavir-boosted) Ritonavir Saquinavir (unboosted) |  | Monitor for adverse reactions. See also Table 5.
Tenofovir disoproxil fumarate |  | Monitor for adverse reactions.
Beta Blockers
Nadolol |  | Monitor for adverse reactions. Concomitant drug dose reduction may be necessary.
Calcium Channel Blockers
Felodipine Nisoldipine |  | Contraindicated during and 2 weeks after TOLSURA treatment.
Diltiazem Other dihydropyridines Verapamil |  | Monitor for adverse reactions. Concomitant drug dose reduction may be necessary. For diltiazem, see also Table 5.
Cardiovascular Drugs, Miscellaneous
Ivabradine Ranolazine |  | Contraindicated during and 2 weeks after TOLSURA treatment.
Aliskiren Riociguat Sildenafil (for pulmonary hypertension) Tadalafil (for pulmonary hypertension) |  | Not recommended during and 2 weeks after TOLSURA treatment. For sildenafil and tadalafil, see also Urologic Drugs below.
Bosentan Guanfacine |  | Monitor for adverse reactions. Concomitant drug dose reduction may be necessary.
Contraceptives
Dienogest Ulipristal |  | Monitor for adverse reactions.
Diuretics
Eplerenone |  | Contraindicated during and 2 weeks after TOLSURA treatment.
Gastrointestinal Drugs
Naloxegol |  | Contraindicated during and 2 weeks after TOLSURA treatment.
Aprepitant Loperamide |  | Monitor for adverse reactions. Concomitant drug dose reduction may be necessary.
Netupitant |  | Monitor for adverse reactions.
Immunosuppressants
Everolimus Sirolimus Temsirolimus (IV) |  | Not recommended during and 2 weeks after TOLSURA treatment.
Budesonide (inhalation) Budesonide (noninhalation) Ciclesonide (inhalation) Cyclosporine (IV) Cyclosporine (non-IV) Dexamethasone | Fluticasone (inhalation) Fluticasone (nasal) Methylprednisolone Tacrolimus (IV) Tacrolimus (oral) | Monitor for adverse reactions. Concomitant drug dose reduction may be necessary.
Lipid-Lowering Drugs
Lomitapide Lovastatin Simvastatin |  | Contraindicated during and 2 weeks after TOLSURA treatment.
Atorvastatin |  | Monitor for drug adverse reactions. Concomitant drug dose reduction may be necessary.
Respiratory Drugs
Salmeterol |  | Not recommended during and 2 weeks after TOLSURA treatment.
SSRIs, Tricyclics and Related Antidepressants
Venlafaxine |  | Monitor for adverse reactions. Concomitant drug dose reduction may be necessary.
Urologic Drugs
Avanafil |  | Contraindicated during and 2 weeks after TOLSURA treatment.
Fesoterodine |  | Patients with moderate to severe renal or hepatic impairment: Contraindicated during and 2 weeks after TOLSURA treatment. Other patients: Monitor for adverse reactions. Concomitant drug dose reduction may be necessary
Solifenacin |  | Patients with severe renal or moderate to severe hepatic impairment: Contraindicated during and 2 weeks after TOLSURA treatment. Other patients: Monitor for adverse reactions. Concomitant drug dose reduction may be necessary.
Darifenacin Vardenafil |  | Not recommended during and 2 weeks after TOLSURA treatment.
Dutasteride Oxybutynin Sildenafil (for erectile dysfunction) Tadalafil (for erectile dysfunction and benign prostatic hyperplasia) Tolterodine |  | Monitor for adverse reactions. Concomitant drug dose reduction may be necessary. For sildenafil and tadalafil, see also Cardiovascular Drugs above.
Miscellaneous Drugs and Other Substances
Colchicine |  | Patients with renal or hepatic impairment: Contraindicated during and 2 weeks after TOLSURA treatment. Other patients: Not recommended during and 2 weeks after TOLSURA treatment.
Eliglustat |  | CYP2D6 EMs [EMs: extensive metabolizers; IMs: intermediate metabolizers, PMs: poor metabolizers.] taking a strong or moderate CYP2D6 inhibitor, CYP2D6 IMs, or CYP2D6 PMs: Contraindicated during and 2 weeks after TOLSURA treatment. CYP2D6 EMsnot taking a strong or moderate CYP2D6 inhibitor: Monitor for adverse reactions. Eliglustat dose reduction may be necessary.
Lumacaftor/Ivacaftor |  | Not recommended 2 weeks before, during, and 2 weeks after TOLSURA treatment.
Alitretinoin (oral) Cabergoline Cannabinoids Cinacalcet Ivacaftor |  | Monitor for adverse reactions. Concomitant drug dose reduction may be necessary.
Vasopressin Receptor Antagonists
Conivaptan Tolvaptan |  | Not recommended during and 2 weeks after TOLSURA treatment.
Drug Interactions with TOLSURA that Decrease Concomitant Drug Concentrations and May Reduce Efficacy of the Concomitant Drug
Antineoplastics
Regorafenib |  | Not recommended during and 2 weeks after TOLSURA treatment.
Gastrointestinal Drugs
Saccharomyces boulardii |  | Not recommended during and 2 weeks after TOLSURA treatment.
Nonsteroidal Anti-Inflammatory Drugs
Meloxicam |  | Concomitant drug dose increase may be necessary.

7.2 Effect of Other Drugs on TOLSURA

Itraconazole is mainly metabolized through CYP3A4. Other substances that either share this metabolic pathway or modify CYP3A4 activity may influence the pharmacokinetics of itraconazole. Some concomitant drugs have the potential to interact with TOLSURA resulting in either increased or sometimes decreased concentrations of TOLSURA. Increased concentrations may increase the risk of adverse reactions associated with TOLSURA. Decreased concentrations may reduce TOLSURA efficacy.

Table 4 lists examples of drugs that may affect itraconazole concentrations, but is not a comprehensive list. Refer to the approved product labeling to become familiar with the interaction pathways, risk potential and specific actions to be taken with regards to each concomitant drug prior to initiating therapy with TOLSURA.

Although many of the clinical drug interactions in Table 5 are based on information with a similar azole antifungal, ketoconazole, these interactions are expected to occur with TOLSURA.

Table 5: Drug Interactions with Other Drugs that Affect TOLSURA Concentrations
Concomitant Drug Within Class | Prevention or Management
Drug Interactions with Other Drugs that Increase TOLSURA Concentrations and May Increase Risk of Adverse Reactions Associated with TOLSURA
Antibacterials
Ciprofloxacin [Based on clinical drug interaction information with itraconazole.] Erythromycin Clarithromycin | Monitor for adverse reactions. TOLSURA dose reduction may be necessary.
Antineoplastics
Idelalisib | Monitor for adverse reactions. TOLSURA dose reduction may be necessary. See also Table 4.
Antivirals
Cobicistat Darunavir (ritonavir-boosted) Elvitegravir (ritonavir-boosted) Fosamprenavir (ritonavir-boosted) Indinavir Ritonavir Saquinavir | Monitor for adverse reactions. TOLSURA dose reduction may be necessary. For, cobicistat, elvitegravir, indinavir, ritonavir, and saquinavir, see also Table 4.
Calcium Channel Blockers
Diltiazem | Monitor for adverse reactions. TOLSURA dose reduction may be necessary. See also Table 4.
Gastrointestinal Drugs
Drugs that reduce gastric acidity e.g. acid neutralizing medicines such as aluminum hydroxide, or acid secretion suppressors such as H2- receptor antagonists and proton pump inhibitors (e.g., omeprazole). | Co-administration of these drugs, including omeprazole, with TOLSURA increases the systemic exposure to itraconazole. Monitor for adverse reactions. TOLSURA dose reduction may be necessary [see Clinical Pharmacology (12.3)].
Drug Interactions with Other Drugs that Decrease TOLSURA Concentrations and May Reduce Efficacy of TOLSURA
Antibacterials
Isoniazid Rifampicin | Not recommended 2 weeks before and during TOLSURA treatment.
Rifabutin | Not recommended 2 weeks before, during, and 2 weeks after TOLSURA treatment. See also Table 4.
Anticonvulsants
Phenobarbital Phenytoin | Not recommended 2 weeks before and during TOLSURA treatment.
Carbamazepine | Not recommended 2 weeks before, during, and 2 weeks after TOLSURA treatment. See also Table 4.
Antivirals
Efavirenz Nevirapine | Not recommended 2 weeks before and during TOLSURA treatment.
Miscellaneous Drugs and Other Substances
Lumacaftor/Ivacaftor | Not recommended 2 weeks before, during, and 2 weeks after TOLSURA treatment.

8 USE IN SPECIFIC POPULATIONS

8.1 Pregnancy

Risk Summary

There are no data on exposure to itraconazole during pregnancy for the approved indications. Published epidemiologic studies of women exposed to short courses of treatment with itraconazole in the first trimester of pregnancy have reported no risk of major birth defects overall and inconclusive findings on the risk of miscarriage (see Data).

In animal reproduction studies, itraconazole was found to cause a dose-related increase in maternal toxicity, embryotoxicity, and teratogenicity in rats at dosage levels of approximately (6-25 times the maximum recommended human dose [MRHD] of 390 mg/day based on mg/kg comparisons), and in mice at dosage levels of approximately 80 mg/kg/day (12 times the MRHD).

All pregnancies have a background risk of birth defect, loss, or other adverse outcomes. The estimated background risk of major birth defects and miscarriage for the indicated populations is unknown. In the U.S. general population, the estimated background risk of major birth defects and miscarriage in clinically recognized pregnancies is 2 to 4% and 15 to 20%, respectively.

Data

Human Data

Published prospective and retrospective cohort studies of women exposed to short courses of treatment with itraconazole in the first trimester of pregnancy (sample size 198-687) have reported no increase in the rate of major birth defects. The most important methodological limitation of these studies is the short duration of exposure in pregnancy (mean duration 6.9 to 8.5 days), or the lack of information on treatment duration. The risk of prolonged exposure in pregnancy is not known.

Published prospective and retrospective cohort studies of pregnant women exposed to itraconazole (sample size 131-198) have reported inconsistent findings on the risk of miscarriage. Available data are inconclusive and limited by possible bias due to earlier enrollment and possible residual confounding in the exposed group compared to the unexposed group.

Animal Data

Itraconazole has been shown to cross the placenta in a rat model. In animal reproduction studies, itraconazole administration to rats and mice during organogenesis resulted in maternal toxicity, embryotoxicity and teratogenicity at and above 40 and 80 mg/kg respectively (doses equivalent to 6- and 12-times the MRHD of 390 mg/day, based on mg/kg comparisons). In rats, the teratogenicity consisted of major skeletal defects; in mice, it consisted of encephaloceles and/or macroglossia.

8.2 Lactation

Risk Summary

Itraconazole is excreted in human milk; however, there are no data on the amount of itraconazole in human milk, the effects on the breastfed child, or the effects on milk production. The developmental and health benefits of breastfeeding should be considered along with the mother's clinical need for TOLSURA and any potential adverse effects on the breastfed child from TOLSURA or from the underlying maternal condition.

8.4 Pediatric Use

Safety and effectiveness in pediatric patients have not been established.

The long-term effects of itraconazole on bone growth in children are unknown. Bone lesions were observed in the young adult rats dosed with oral itraconazole for 3 to 12 months [see Nonclinical Toxicology (13.2)].

8.5 Geriatric Use

Clinical studies of itraconazole did not include sufficient numbers of subjects aged 65 years and over to determine whether they respond differently from younger subjects. It is advised to use TOLSURA Capsules in these patients only if it is determined that the potential benefit outweighs the potential risks. In general, it is recommended that the dose selection for an elderly patient should be taken into consideration, reflecting the greater frequency of decreased hepatic, renal, or cardiac function, and of concomitant disease or other drug therapy.

Reversible or permanent hearing loss has been reported in elderly patients receiving treatment with itraconazole. Several of these reports included concurrent administration of quinidine which is contraindicated [see Boxed Warning, Contraindications (4.1) and Drug Interactions (7.1)].

8.6 Renal Impairment

Limited data are available on the use of oral itraconazole in patients with renal impairment. It is recommended that patients with renal impairment be carefully monitored when taking TOLSURA [see Clinical Pharmacology (12) and Warnings and Precautions (5.1)].

8.7 Hepatic Impairment

Limited data are available on the use of oral itraconazole in patients with hepatic impairment. It is recommended that patients with impaired hepatic function be carefully monitored when taking TOLSURA. It is recommended that the prolonged elimination half-life of itraconazole observed in the single oral dose clinical trial with itraconazole capsules in cirrhotic patients be considered when deciding to initiate therapy with other medications metabolized by CYP3A4 [see Clinical Pharmacology (12.3)].

In patients with elevated or abnormal liver enzymes or active liver disease, or who have experienced liver toxicity with other drugs, treatment with TOLSURA is strongly discouraged unless there is a serious or life-threatening situation where the expected benefit exceeds the risk. It is recommended that liver function monitoring be done in patients with pre-existing hepatic function abnormalities or those who have experienced liver toxicity with other medications [see Clinical Pharmacology (12) and Warnings and Precautions (5.2)].

10 OVERDOSAGE

Itraconazole is not removed by dialysis. In the event of accidental overdosage, supportive measures should be employed. Activated charcoal may be given if considered appropriate.

11 DESCRIPTION

TOLSURA (itraconazole capsules) is an azole antifungal drug for oral use. Itraconazole is an equal mixture of four diastereomers (two enantiomeric pairs), each possessing three chiral centers. It may be represented by the following structural formula and nomenclature:

(±)-1-[(R*)-sec-butyl]-4-[p-[4-[p-[[(2R*,4S*)-2-(2,4-dichlorophenyl)-2-(1H-1,2,4-triazol-1-ylmethyl)-1,3-dioxolan-4-yl]methoxy]phenyl]-1-piperazinyl]phenyl]-Δ^2-1,2,4-triazolin-5-one mixture with (±)-1-[(R*)-sec-butyl]-4-[p-[4-[p-[[(2S*,4R*)-2-(2,4-dichlorophenyl)-2-(1H-1,2,4-triazol-1-ylmethyl)-1,3-dioxolan-4-yl]methoxy]phenyl]-1-piperazinyl]phenyl]-Δ^2-1,2,4-triazolin-5-one

or

(±)-1-[(RS)-sec-butyl]-4-[p-[4-[p-[[(2R,4S)-2-(2,4-dichlorophenyl)-2-(1H-1,2,4-triazol-1-ylmethyl)-1,3-dioxolan-4-yl]methoxy]phenyl]-1-piperazinyl]phenyl]-Δ^2-1,2,4-triazolin-5-one.

Itraconazole has a molecular formula of C35H38Cl2N8O4 and a molecular weight of 705.64. It is a white to slightly yellowish powder. It is insoluble in water, very slightly soluble in alcohols, and freely soluble in dichloromethane. It has a pKa of 3.70 (based on extrapolation of values obtained from methanolic solutions) and a log (n-octanol/water) partition coefficient of 5.66 at pH 8.1.

Each TOLSURA capsule contains 65 mg of itraconazole dispersed in a polymer matrix and encapsulated in a hard gelatin capsule. The inactive ingredients are colloidal silicon dioxide, hypromellose phthalate, magnesium stearate and sodium starch glycolate.

12 CLINICAL PHARMACOLOGY

12.1 Mechanism of Action

Itraconazole is an azole antifungal drug [see Microbiology (12.4)].

12.3 Pharmacokinetics

General Pharmacokinetic Characteristics

The steady-state pharmacokinetics of itraconazole following administration of a 130 mg twice daily dose regimen of TOLSURA (2 × 65 mg) was compared with a 200 mg twice daily dose regimen of itraconazole capsules (2 × 100 mg) immediately after a meal for 14.5 days in 16 healthy volunteers; the results from this study are presented in Table 6 below

Table 6: Pharmacokinetics of Itraconazole Following Administration of TOLSURA and Itraconazole Capsules Given Twice Daily for 14.5 Days Under Fed Conditions [Standardized high-fat, high-calorie breakfast was given 30 minutes prior to dosing on the morning of Day 15; standardized meals given prior to all other doses.] in 16 Healthy Subjects
Parameter [Geometric means ± standard deviation] , [Tmax presented as median (range)] | TOLSURA 130 mg twice daily (2 × 65 mg Capsules) | Itraconazole 200 mg twice daily (2 × 100 mg Capsules)
AUC0-tau (hr*mcg/ml) | 15.6 ± 3.7 | 14.9 ±3.8
Ctrough (mcg/ml) | 1.2 ±0.4 | 1.0±0.3
Cmax,ss (mcg/ml) | 1.6 ±0.4 | 1.5 ±0.4
Tmax,ss (h) | 7.0 (1-10) | 5.0 (1-8)

Peak plasma concentrations of itraconazole after administration of a single dose of TOLSURA are reached within 2 to 6 hours following oral administration in either the fasted or fed states. As a consequence of non-linear pharmacokinetics, itraconazole accumulates in plasma during multiple dosing of TOLSURA. Steady-state concentrations are generally reached within about 15 days, with mean Cmax values of 0.6 mcg/ml and 1.7 mcg/ml after oral administration of 130 mg once daily and 130 mg twice daily, respectively

Absorption

Effect of Food

The effect of food on the steady-state pharmacokinetics of itraconazole following administration of a 130 mg twice daily dose regimen of TOLSURA (2 × 65 mg) for 14.5 days under fed and fasted conditions was evaluated in 20 healthy volunteers. A high-fat meal with total caloric content of 919 calories (526 fat calories, 260 carbohydrate calories and 133 protein calories) was used in the study. The results are shown in Table 7 below.

Table 7: Pharmacokinetic Parameters of Itraconazole Following Administration of TOLSURA 130 mg (2 × 65 mg capsules) Given Twice Daily for 14.5 Days Under Fed and Fasted Conditions in 20 Healthy Subjects
Parameter | Treatment | Geometric Mean | Fed/Fasted Ratio (%) | 90% Confidence Interval
Cmax_ss (mcg/mL) | Fed | 1.4 ± 0.6 | 73.7 | 69.0, 77.3
Cmax_ss (mcg/mL) | Fasted | 1.9 ± 0.9
Ctrough,ss (mcg/mL) | Fed | 1.0 ± 0.3 | 90.0 | 86.4, 97.0
Ctrough,ss (mcg/mL) | Fasted | 1.1 ± 0.6
AUCtau (hr*mcg/mL) | Fed | 13.4 ± 5.0 | 78.4 | 74.5, 81.9
AUCtau (hr*mcg/mL) | Fasted | 17.1 ± 8.0
 |  | Median | Range
Tmax (hr) | Fed | 4.00 | 0.5 to 10
Tmax (hr) | Fasted | 3.50 | 0.5 to 5

Distribution

Most of the itraconazole in plasma is bound to protein (99.8%), with albumin being the main binding component (99.6% for the hydroxy-metabolite). It has also a marked affinity for lipids. Only 0.2% of the itraconazole in plasma is present as free drug. Itraconazole is distributed in a large apparent volume in the body (>700 L), suggesting extensive distribution into tissues. Concentrations in lung, kidney, liver, bone, stomach, spleen and muscle were found to be two to three times higher than corresponding concentrations in plasma, and the uptake into keratinous tissues, skin in particular, up to four times higher. Concentrations in the cerebrospinal fluid are much lower than in plasma.

Elimination

The terminal half-life of itraconazole following repeated dose administration of TOLSURA ranges between 34 to 42 hours under fed conditions.

Metabolism

Itraconazole is extensively metabolized by the liver into a large number of metabolites. In vitro studies have shown that CYP3A4 is the major enzyme involved in the metabolism of itraconazole. The main metabolite is hydroxy-itraconazole, which has in vitro antifungal activity comparable to itraconazole; trough plasma concentrations of this metabolite are about twice those of itraconazole.

Excretion

Itraconazole is excreted mainly as inactive metabolites in urine (35%) and in feces (54%) within one week of an oral solution dose. Renal excretion of itraconazole and the active metabolite hydroxyitraconazole account for less than 1% of an intravenous dose. Based on an oral radiolabeled dose, fecal excretion of unchanged drug ranges from 3% to 18% of the dose.

As re-distribution of itraconazole from keratinous tissues appears to be negligible, elimination of itraconazole from these tissues is related to epidermal regeneration. Contrary to plasma, the concentration in skin persists for 2 to 4 weeks after discontinuation of a 4-week treatment and in nail keratin - where itraconazole can be detected as early as 1 week after start of treatment - for at least six months after the end of a 3-month treatment period.

Specific Populations

Patients with Renal Impairment

Limited data are available on the use of oral itraconazole in patients with renal impairment. A pharmacokinetic study using a single 200-mg oral dose of itraconazole was conducted in three groups of patients with renal impairment (uremia: n=7; hemodialysis: n=7; and continuous ambulatory peritoneal dialysis: n=5). In uremic subjects with a mean creatinine clearance of 13 mL/min. × 1.73 m^2, the exposure, based on AUC, was slightly reduced compared with normal population parameters. This study did not demonstrate any significant effect of hemodialysis or continuous ambulatory peritoneal dialysis on the pharmacokinetics of itraconazole (tmax, Cmax, and AUC0-8h). Plasma concentration versus-time profiles showed wide intersubject variation in all three groups. After a single intravenous versus-time profiles showed wide intersubject variation in all three groups.

After a single intravenous dose, the mean terminal half-lives of itraconazole in patients with mild (defined in this study as CrCl 50-79 ml/min), moderate (defined in this study as CrCl 20-49 ml/min), and severe renal impairment (defined in this study as CrCl <20 ml/min) were similar to that in healthy subjects (range of means 42-49 hours vs 48 hours in renally impaired patients and healthy subjects, respectively). Overall exposure to itraconazole, based on AUC, was decreased in patients with moderate and severe renal impairment by approximately 30% and 40%, respectively, as compared with subjects with normal renal function. Data are not available in renally impaired patients during long-term use of itraconazole. Dialysis has no effect on the half-life or clearance of itraconazole or hydroxy-itraconazole.

Patients with Hepatic Impairment

Itraconazole is predominantly metabolized in the liver. A pharmacokinetic study was conducted in 6 healthy and 12 cirrhotic subjects who were administered a single 100-mg dose of itraconazole capsules. A statistically significant reduction in mean Cmax (47%) and a twofold increase in the elimination half-life (37 ± 17 hours vs. 16 ± 5 hours) of itraconazole were noted in cirrhotic subjects compared with healthy subjects. However, overall exposure to itraconazole, based on AUC, was similar in cirrhotic patients and in healthy subjects. Data are not available in cirrhotic patients during long-term use of itraconazole.

Drug Interaction Studies

Omeprazole

The effect of multiple daily oral 40 mg doses (steady-state conditions) of the proton pump inhibitor, omeprazole, on the exposure to itraconazole from a single 130 mg dose of TOLSURA (2 × 65 mg capsules) when dosed under fasted conditions was evaluated in 30 healthy adult subjects. As illustrated in Table 8 below, the mean itraconazole AUC∞ was 22% higher and mean Cmax 31% higher when TOLSURA was co-administered with omeprazole.

Table 8: Pharmacokinetics of Itraconazole Following Single Dose Administration of TOLSURA 130 mg (2 × 65mg capsules) Alone or with Omeprazole 40 mg QD Administered for 7 Days Under Fasted Conditions in Healthy Volunteers
Parameter | Treatment A [Treatment A: TOLSURA] Mean ±SD | Treatment A + B [Treatment B: Omeprazole] Mean ±SD | Treatment A+B vs Treatment A Ratio % | 90% Confidence Interval
AUC∞ (h∙ng/mL) | 2846.3 ±1644.4 | 3477.9 ± 1572.6 | 122.2 | 108.7, 137.3
Cmax (ng/mL) | 212.9 ± 119.1 | 278.8 ±106.8 | 130.9 | 111.4, 153.8
Tmax [Tmax is given as median (Range)] (h) | 3.5 (2.0 -5.0) | 3.3 (1.5 – 5.0) | - | -

12.4 Microbiology

Mechanism of Action

In vitro studies have demonstrated that itraconazole inhibits the cytochrome P450-dependent, ^14C-demethylation of ergosterol, which is a vital component of fungal cell membranes.

Resistance

Isolates from several fungal species with decreased susceptibility to itraconazole have been isolated in vitro and from patients receiving prolonged therapy. Several in vitro studies have reported that some fungal clinical isolates with reduced susceptibility to one azole antifungal agent may also be less susceptible to other azole derivatives. The finding of cross-resistance is dependent on a number of factors, including the species evaluated, its clinical history, the particular azole compounds compared, and the type of susceptibility test performed.

Itraconazole is not active against Zygomycetes (e.g., Rhizopus spp., Rhizomucor spp., Mucor spp. and Absidia spp.), Fusarium spp., Scedosporium spp. and Scopulariopsis spp.

Interaction with Other Antimicrobials

Studies (both in vitro and in vivo) suggest that the activity of amphotericin B may be suppressed by prior azole antifungal therapy. Ergosterol is the active site for amphotericin B. In one study, the antifungal activity of amphotericin B against Aspergillus fumigatus infections in mice was inhibited by ketoconazole therapy. The clinical significance of this finding is unknown.

Antifungal Activity

Itraconazole exhibits in vitro activity against Blastomyces dermatitidis, Histoplasma capsulatum, Histoplasma duboisii, Aspergillus flavus, Aspergillus fumigatus, and Trichophyton species [see Indications and Usage (1)]. Correlation between minimum inhibitory concentration (MIC) results in vitro and clinical outcome has yet to be established for azole antifungal agents.

13 NONCLINICAL TOXICOLOGY

13.1 Carcinogenesis, Mutagenesis, Impairment of Fertility

Carcinogenesis

Itraconazole showed no evidence of carcinogenicity potential in mice treated orally for 23 months at dosage levels up to 80 mg/kg/day (approximately 12×MRHD, based on mg/kg comparisons). Male rats treated with 25 mg/kg/day (4×MRHD) had a slightly increased incidence of soft tissue sarcoma. These sarcomas may have been a consequence of hypercholesterolemia, which is a response of rats, but not dogs or humans, to chronic itraconazole administration. Female rats treated with 50 mg/kg/day (8×MRHD) had an increased incidence of squamous cell carcinoma of the lung (2/50) as compared to the untreated group. Although the occurrence of squamous cell carcinoma in the lung is extremely uncommon in untreated rats, the increase in this study was not statistically significant.

Mutagenesis

Itraconazole produced no mutagenic effects when assayed in DNA repair test (unscheduled DNA synthesis) in primary rat hepatocytes, in Ames tests with Salmonella typhimurium (6 strains) and Escherichia coli, in the mouse lymphoma gene mutation tests, in a sex-linked recessive lethal mutation (Drosophila melanogaster) test, in chromosome aberration tests in human lymphocytes, in a cell transformation test with C3H/10T½ C18 mouse embryo fibroblasts cells, in a dominant lethal mutation test in male and female mice, and in micronucleus tests in mice and rats.

Impairment of Fertility

Itraconazole did not affect the fertility of male or female rats treated orally with dosage levels of up to 40 mg/kg/day (6×MRHD, based on mg/kg comparisons), even though parental toxicity was present at this dosage level.

13.2 Animal Toxicology and/or Pharmacology

When itraconazole was administered intravenously to anesthetized dogs, a dose-related negative inotropic effect was documented.

In three toxicology studies using rats, itraconazole (dosed in feed or via oral gavage) induced bone defects at dosage levels as low as 20 mg/kg/day (3×MRHD, based on mg/kg comparisons). The induced defects included reduced bone plate activity, thinning of the zona compacta of the large bones, and increased bone fragility. At a dosage level of 80 mg/kg/day (12×MRHD) over 1 year or 160 mg/kg/day (25×MRHD) for 6 months, itraconazole induced small tooth pulp with hypocellular appearance in some rats.

14 CLINICAL STUDIES

Overview of the Clinical Studies

Clinical studies in invasive mycoses listed in this section were conducted with itraconazole 100 mg capsules. Dosage for TOLSURA is different from that of other itraconazole formulations. TOLSURA is not interchangeable or substitutable with other itraconazole products [see Indications and Usage (1), Dosage and Administration (2) and Clinical Pharmacology (12.3)]

14.1 Blastomycosis

Analyses were conducted on data from two open-label, non-concurrently controlled studies (N=73 combined) in patients with normal or abnormal immune status treated with the100 mg itraconazole capsules. The median dose was 200 mg/day (2 × 100 mg). A response for most signs and symptoms was observed within the first 2 weeks, and all signs and symptoms cleared between 3 and 6 months. Results of these two studies demonstrated substantial evidence of the effectiveness of itraconazole for the treatment of blastomycosis compared with the natural history of untreated cases.

14.2 Histoplasmosis

Analyses were conducted on data from two open-label, non-concurrently controlled studies (N=34 combined) in patients with normal or abnormal immune status (not including HIV-infected patients) treated with the 100 mg itraconazole capsules. The median dose was 200 mg/day (2 × 100 mg). A response for most signs and symptoms was observed within the first 2 weeks, and all signs and symptoms cleared between 3 and 12 months. Results of these two studies demonstrated substantial evidence of the effectiveness of itraconazole for the treatment of histoplasmosis, compared with the natural history of untreated cases.

14.3 Histoplasmosis in HIV-infected Patients

Data from a small number of HIV-infected patients treated with the 100 mg itraconazole capsules suggested that the response rate of histoplasmosis in HIV-infected patients is similar to that of non-HIV-infected patients. The clinical course of histoplasmosis in HIV-infected patients is more severe and usually requires maintenance therapy to prevent relapse.

14.4 Aspergillosis

Analyses were conducted on data from an open-label, "single-patient-use" protocol designed to make itraconazole available in the U.S. for patients who either failed or were intolerant of amphotericin B therapy (N=190). The findings were corroborated by two smaller open-label studies (N=31 combined) in the same patient population. Most adult patients were treated with a daily dose of 200 (2 × 100 mg) to 400 (4 × 100 mg) mg, with a median duration of 3 months. Results of these studies demonstrated substantial evidence of effectiveness of the 100 mg itraconazole capsules as a second-line therapy for the treatment of aspergillosis compared with the natural history of the disease in patients who either failed or were intolerant of amphotericin B therapy.

16 HOW SUPPLIED/STORAGE AND HANDLING

TOLSURA (itraconazole capsules) is supplied in a size 1, hard gelatin capsules with light blue cap and white body, imprinted with "i-65" in black on the cap and containing 65 mg of itraconazole.

TOLSURA capsules are supplied as follows:

Bottles of 8 capsules | Bottles of 60 capsules
NDC 51862-462-88 | NDC 51862-462-60

STORAGE AND HANDLING

Store at 25°C (77°F); excursions permitted 15°C to 30°C (59°F to 86°F) [see USP Controlled Room Temperature]. Dispense in a tight, light resistant container.

17 PATIENT COUNSELING INFORMATION

Advise the patient to read the FDA-approved patient labeling (Patient Information).

Important Administration Instructions

Instruct the patients that TOLSURA:

- Cannot be interchanged or substituted with other itraconazole products.
- Must be swallowed whole and administered with food.

Congestive Heart Failure

Inform patients about the signs and symptoms of congestive heart failure. Instruct them to discontinue TOLSURA and contact their healthcare provider immediately, if these signs or symptoms occur during TOLSURA administration [see Warnings and Precautions (5.1)].

Hepatoxicity

Instruct patients to stop TOLSURA treatment immediately and contact their healthcare provider if any signs and symptoms suggestive of liver dysfunction develop. Such signs and symptoms may include unusual fatigue, anorexia, nausea and/or vomiting, jaundice, dark urine, or pale stools [see Warnings and Precautions (5.2)].

Use with Proton Pump Inhibitors and Potential Drug Interactions

Advise patients to discuss with their physician the use of TOLSURA with proton pump inhibitors, such as omeprazole. Instruct patients to contact their physician before taking any other concomitant medications with TOLSURA to ensure there are no potential drug interactions [see Contraindications (4.1, 4.2), Warnings and Precautions (5.5) and Drug interactions (7.2)].

Hearing Loss

Instruct patients that hearing loss can occur with the use of TOLSURA. The hearing loss usually resolves when treatment is stopped but can persist in some patients. Advise patients to inform their healthcare provider if any hearing loss symptoms occur [see Warnings and Precautions (5.7)].

Vision Problem

Instruct patients that dizziness or blurred/double vision can sometimes occur with TOLSURA. Advise patients that if they experience these dizziness or blurred/double vision, they should contact their healthcare provider, and instruct the patient not to drive or use machines [see Adverse Reactions (6.1)].

Pregnancy

Advise patients to notify their physician if they become pregnant or intend to become pregnant during therapy [see Use in Specific Populations (8.1)].

Mayne Pharma

Raleigh, NC 27609

TOLSURA is a registered trademark of Mayne Pharma.

Patient Information
TOLSURA (tol sur ah)
(itraconazole capsules)

Read this Patient Information that comes with TOLSURA before you start taking it and each time you get a refill. There may be new information. This information does not take the place of talking with your doctor about your medical condition or your treatment.

What is the most important information I should know about TOLSURA?
TOLSURA can cause serious side effects, including:

1. Congestive heart failure. TOLSURA can cause congestive heart failure or make congestive heart failure that you already have worse. Stop taking TOLSURA and call your doctor right away if you have any of these symptoms of congestive heart failure:

- shortness of breath
- swelling of your feet, ankles or legs
- sudden weight gain
- increased tiredness

- coughing up white or pink mucus (phlegm)
- fast heartbeat
- waking up at night more than normal for you

2. Heart problems and other serious medical problems. Serious medical problems that affect the heart and other parts of your body can happen if you take TOLSURA with certain other medicines.

- Do not take TOLSURA if you take any of the following medicines:

- avanafil
- disopyramide
- dofetilide
- dronedarone
- eplerenone
- ergot alkaloids (such as dihydroergotamine or ergotamine)
- felodipine
- irinotecan
- isavuconazonium
- ivabradine
- lomitapide

- lovastatin
- lurasidone
- methadone
- midazolam (taken by mouth)
- naloxegol
- nisoldipine
- pimozide
- quinidine
- ranolazine
- simvastatin
- ticagrelor
- triazolam

- Do not take TOLSURA if you have kidney or liver problems and take any of the following medicines:
  - colchicine
  - fesoterodine
  - solifenacin
- Do not take TOLSURA:
  - if you have been told that an enzyme in your body, called CYP2D6, breaks down (metabolizes) certain medicines in your body too slowly.
  - if you are taking the medicine eliglustat and are also taking a medicine that slows the rate that your body breaks down (metabolizes) certain other medicines (CYP2D inhibitor). Ask your doctor or pharmacist if you take any of these medicines.

These are not complete lists of medicines that can interact with TOLSURA. TOLSURA may affect the way other medicines work, and other medicines may affect how TOLSURA works. You can ask your pharmacist for a list of medicines that interact with TOLSURA.
Before you start taking TOLSURA, tell your doctor about all the medicines you take, including prescription and over-the-counter medicines, vitamins, and herbal supplements.
Before you start any new medicine, ask your doctor or pharmacist if it is safe to take it with TOLSURA or within 2 weeks after stopping treatment with TOLSURA.

3. Liver problems. TOLSURA can cause serious liver problems which may be severe and lead to death. Stop taking TOLSURA and call your doctor right away if you have any of these symptoms of liver problems:

- unusual fatigue
- loss of appetite
- nausea or vomiting

- your skin or the white part of your eyes turn yellow (jaundice)
- dark (tea-colored) urine
- light-colored stools (bowel movement)

For more information about side effects, see "What are the possible side effects of TOLSURA?"

What is TOLSURA?
TOLSURA is a prescription medicine used to treat the following fungal infections in adults: blastomycosis, histoplasmosis, and aspergillosis.
TOLSURA is not for use for the treatment of fungal infections of the toenails or fingernails (onychomycosis).
TOLSURA is not for use in place of other medicines that contain itraconazole.
It is not known if TOLSURA is safe and effective in children.

Do not take TOLSURA if you:

- See "What is the most important information I should know about TOLSURA?"
- are allergic to itraconazole or any of the ingredients in TOLSURA. See the end of this Patient Information leaflet for a complete list of ingredients in TOLSURA.

Before taking TOLSURA, tell your doctor about all of your medical conditions, including if you:

- have heart problems.
- have lung problems.
- have kidney problems.
- have liver problems.
- have had an allergic reaction to a medicine used to treat a fungal infection.
- are pregnant or plan to become pregnant. It is not known if TOLSURA will harm your unborn baby. Tell your doctor if you become pregnant during treatment with TOLSURA.
- are breastfeeding or plan to breastfeed. TOLSURA can pass into your breast milk. Talk to your doctor about the best way to feed your baby if you take TOLSURA.

Before you start taking TOLSURA, tell your doctor about all the medicines you take, including prescription and over-the-counter medicines, vitamins, and herbal supplements.
Especially tell your doctor if you take:

- a medicine to treat high blood pressure or certain other heart problems called a calcium channel blocker.
- a medicine to reduce acid in your stomach called a proton pump inhibitor, such as omeprazole.

How should I take TOLSURA?

- Take TOLSURA exactly as prescribed by your doctor. Your doctor will tell you how much TOLSURA to take and when to take it.
- TOLSURA must be taken with food.
- TOLSURA capsules must be swallowed whole.
- Do not chew, crush or break TOLSURA capsules.
- If you take too much TOLSURA, call your doctor or go to the nearest hospital emergency room right away.

What should I avoid while taking TOLSURA?

- TOLSURA can cause dizziness and vision problems. Do not drive or operate machinery until you know how TOLSURA affects you. Tell your doctor if you get dizziness or vision problems.

What are the possible side effects of TOLSURA?
TOLSURA may cause serious side effects, including:

- See "What is the most important information I should know about TOLSURA?"
- New or worsening high blood pressure and low potassium levels in your blood (pseudoaldosteronism). Your healthcare provider should check your blood pressure and potassium levels.
- Nerve problems (neuropathy). Nerve problems have happened in some people who have taken TOLSURA for longer than 3 months. Call your doctor right away if you have tingling or numbness in your hands or feet. Your doctor may stop your treatment with TOLSURA if you have nerve problems.
- Hearing loss. Hearing loss can happen in some people who take TOLSURA. Hearing loss usually improves when treatment with TOLSURA is stopped, but hearing loss has been permanent in some people. Call your doctor if you have any changes in your hearing.

The most common side effects of TOLSURA include:

- nausea
- rash
- vomiting
- swelling
- headache
- diarrhea
- fatigue

- fever
- itching
- high blood pressure
- abnormal liver blood tests
- stomach pain
- dizziness
- low blood potassium levels

- loss of appetite
- general feeling of discomfort
- decreased sex drive
- sleepiness
- elevated levels of a type of protein, called albumin, in your urine
- erectile dysfunction

These are not all the possible side effects of TOLSURA.
Call your doctor for medical advice about side effects. You may report side effects to FDA at 1-800-FDA-1088.

How should I store TOLSURA?

- Store TOLSURA at room temperature between 68°F to 77°F (20°C to 25°C).
- Keep TOLSURA in a tightly closed container.
- Keep TOLSURA away from light.

Keep TOLSURA and all medicines out of the reach of children.

General information about the safe and effective use of TOLSURA.
Medicines are sometimes prescribed for purposes other than those listed in a Patient Information leaflet. Do not use TOLSURA for a condition for which it was not prescribed. Do not give TOLSURA to other people, even if they have the same symptoms that you have. It may harm them.
You can ask your doctor or pharmacist for information about TOLSURA that is written for health professionals.

What are the ingredients in TOLSURA?
Active ingredient: itraconazole
Inactive ingredients: colloidal silicon dioxide, hypromellose phthalate, magnesium stearate and sodium starch glycolate
Manufactured by: Mayne Pharma
For more information, go to www.maynepharma.com or call 1-844-825-8500

This Patient Information has been approved by the U.S. Food and Drug Administration.
Issued: 10/2024

PRINCIPAL DISPLAY PANEL - 65 mg Capsule Bottle Label

NDC 51862-462-60

TOLSURA®
(Itraconazole Capsules)

65 mg

Attention: Tolsura® is NOT
interchangeable on a mg per mg basis
with other formulations of itraconazole.

Rx Only
60 Capsules

mayne pharma